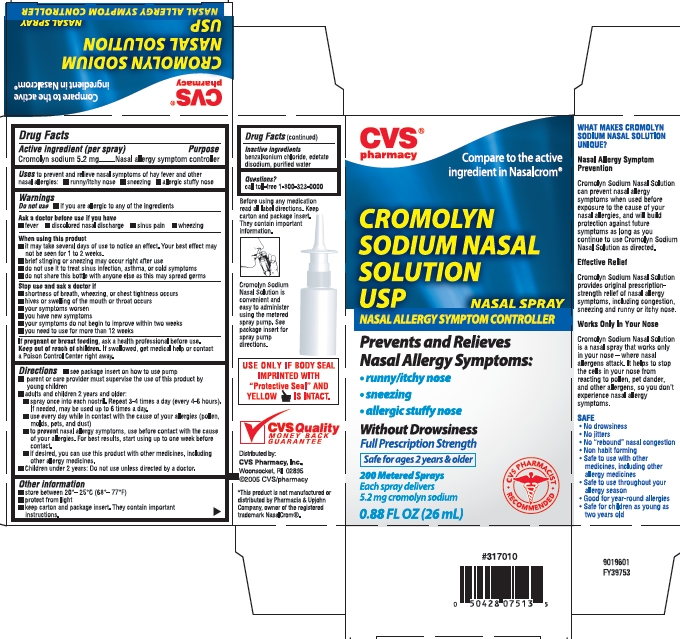 DRUG LABEL: Cromolyn Sodium
NDC: 59779-075 | Form: SPRAY, METERED
Manufacturer: CVS Pharmacy
Category: otc | Type: HUMAN OTC DRUG LABEL
Date: 20111219

ACTIVE INGREDIENTS: CROMOLYN SODIUM 5.2 mg/1 mL
INACTIVE INGREDIENTS: BENZALKONIUM CHLORIDE; EDETATE DISODIUM; WATER

Cromolyn Sodium Nasal Solution USP
NASAL SPRAY

Active ingredient (per spray)

Cromolyn sodium 5.2 mg

Purpose

Nasal allergy symptom controller

Uses

to prevent and relieve nasal symptoms of hay fever and other nasal allergies:

- runny/itchy nose
- sneezing
- allergic stuffy nose

Warnings

Do not use

- if you are allergic to any of the ingredients

Ask a doctor before use if you have

- fever
- discolored nasal discharge
- sinus pain
- wheezing

When using this product

- it may take several days of use to notice an effect. Your best effect may not be seen for 1 to 2 weeks.
- brief stinging or sneezing may occur right after use
- do not use it to treat sinus infection, asthma, or cold symptoms
- do not share this bottle with anyone else as this may spread germs

Stop use and ask a doctor if

- shortness of breath, wheezing, or chest tightness occurs
- hives or swelling of the mouth or throat occurs
- your symptoms worsen
- you have new symptoms
- your symptoms do not begin to improve within two weeks
- you need to use for more than 12 weeks

If pregnant or breast feeding, ask a health professional before use.

Keep out of reach of children.

If swallowed, get medical help or contact a Poison Control Center right away.

Directions

- see package insert on how to use pump
- parent or care provider must supervise the use of this product by young children
- adults and children 2 years and older:
  - spray once into each nostril. Repeat 3-4 times a day (every 4-6 hours). If needed, may be used up to 6 times a day.
  - use every day while in contact with the cause of your allergies (pollen, molds, pets, and dust)
  - to prevent nasal allergy symptoms, use before contact with the cause of your allergies. For best results, start using up to one week before contact.
  - if desired, you can use this product with other medicines, including other allergy medicines.
- Children under 2 years: Do not use unless directed by a doctor.

Other information

- store between 20°– 25°C (68°– 77°F)
- protect from light
- keep carton and package insert. They contain important instructions.

Inactive ingredients

benzalkonium chloride, edetate disodium, purified water

Questions?

call toll free 1-800-323-0000.

Before using any medication read all label directions. Keep carton and packaging insert. They contain important information.

Cromolyn Sodium Nasal Solution is convenient and easy to administer using the metered spray pump. See package insert for spray pump directions.

USE ONLY IF BODY SEAL IMPRINTED WITH "Protective Seal" AND YELLOW IS INTACT.

CVS Quality MONEY BACK GURANTEE

Distributed by:
CVS Pharmacy Inc.,

Woonsocket, RI 02895
©2005 CVS/pharmacy

*This product is not manufactured or distributed by Pharmacia & Upjohn Company, owner of the registered trademark NasalCrom®.

Package/Label Principal Display Panel

CVS pharmacy®

Compare to the active ingredient in Nasalcrom®

CROMOLYN SODIUM NASAL SOLUTION USP

NASAL SPRAY

NASAL ALLERGY SYMPTOM CONTROLLER

Prevents and Relieves Nasal Allergy Symptoms:
runny/itchy nose
sneezing
allergic stuffy nose

Without Drowsiness

Full Prescription Strength

Safe For Ages 2 Years & Older
CVS PHARAMACIST RECOMMENDED

200 Metered Sprays

Each spray delivers

5.2 mg cromolyn sodium

0.88 FL OZ (26 mL)